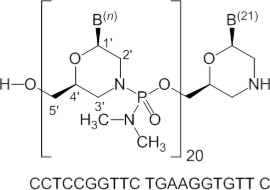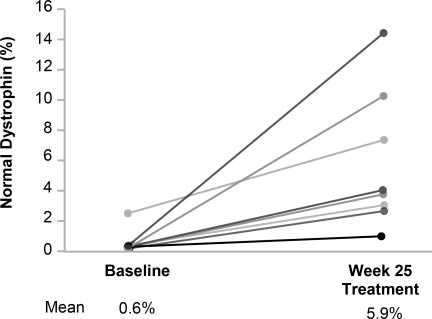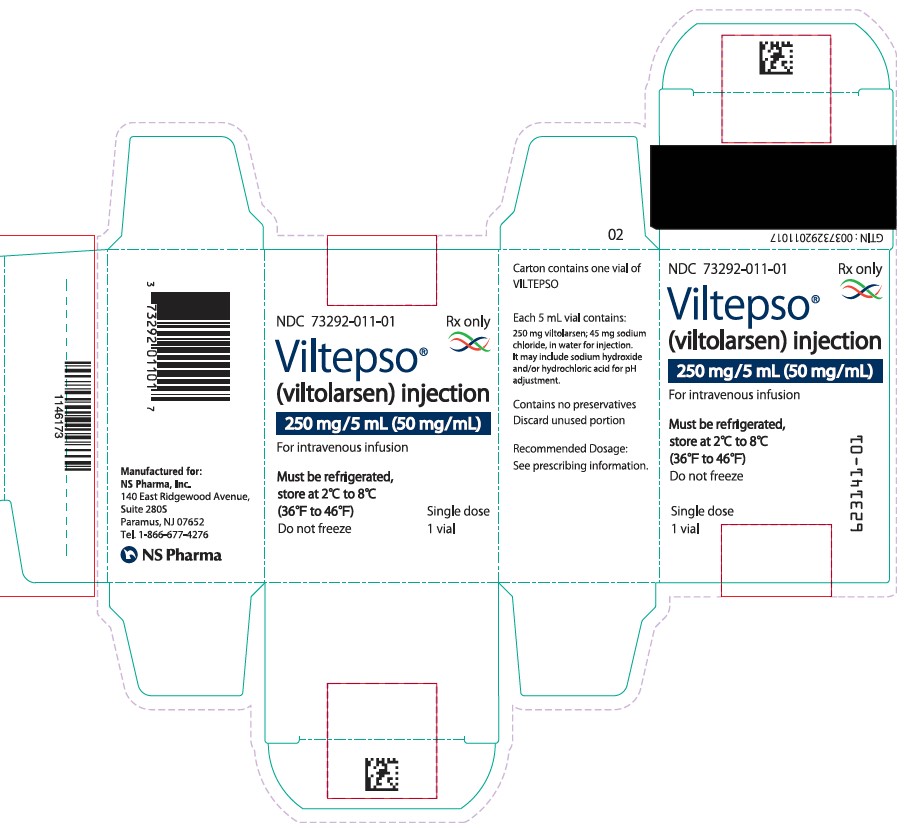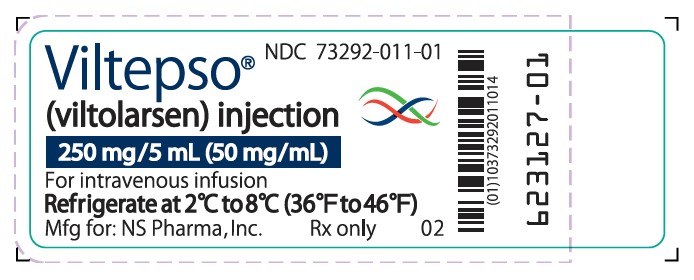 DRUG LABEL: Viltepso
NDC: 73292-011 | Form: INJECTION, SOLUTION
Manufacturer: NS Pharma, Inc.
Category: prescription | Type: HUMAN PRESCRIPTION DRUG LABEL
Date: 20250716

ACTIVE INGREDIENTS: viltolarsen 250 mg/1 1
INACTIVE INGREDIENTS: sodium chloride; hydrochloric acid; sodium hydroxide; water

HIGHLIGHTS OF PRESCRIBING INFORMATION

These highlights do not include all the information needed to use VILTEPSO® safely and effectively. See full prescribing information for VILTEPSO.
VILTEPSO (viltolarsen) injection, for intravenous use
Initial U.S. Approval: 2020

RECENT MAJOR CHANGES

Dosage and Administration (2.1), Monitoring to Assess Safety | 3/2021
Warnings and Precautions (5.1), Kidney Toxicity | 3/2021

1 INDICATIONS AND USAGE

VILTEPSO is an antisense oligonucleotide indicated for the treatment of Duchenne muscular dystrophy (DMD) in patients who have a confirmed mutation of the DMD gene that is amenable to exon 53 skipping. This indication is approved under accelerated approval based on an increase in dystrophin production in skeletal muscle observed in patients treated with VILTEPSO. Continued approval for this indication may be contingent upon verification and description of clinical benefit in a confirmatory trial. (1)

2 DOSAGE AND ADMINISTRATION

- Serum cystatin C, urine dipstick, and urine protein-to-creatinine ratio should be measured before starting VILTEPSO. (2.1)
- Recommended dosage is 80 milligrams per kilogram of body weight once weekly. (2.2)
- Administer as an intravenous infusion over 60 minutes. (2.2, 2.4)
- If the volume of VILTEPSO required is less than 100 mL, dilution in 0.9% Sodium Chloride Injection, USP, is required. (2.3)

3 DOSAGE FORMS AND STRENGTHS

Injection: 250 mg/5 mL (50 mg/mL) in a single-dose vial (3)

4 CONTRAINDICATIONS

None (4)

5 WARNINGS AND PRECAUTIONS

Kidney Toxicity: Based on animal data, may cause kidney toxicity. Kidney function should be monitored; creatinine may not be a reliable measure of renal function in DMD patients. (5.1, 13.2)

6 ADVERSE REACTIONS

The most common adverse reactions (incidence ≥15% in patients treated with VILTEPSO) were upper respiratory tract infection, injection site reaction, cough, and pyrexia. (6.1)

To report SUSPECTED ADVERSE REACTIONS, contact NS Pharma at 1-866 NSPHARM (1-866-677-4276) or FDA at 1-800-FDA-1088 or www.fda.gov/medwatch.

FULL PRESCRIBING INFORMATION

1 INDICATIONS AND USAGE

VILTEPSO is indicated for the treatment of Duchenne muscular dystrophy (DMD) in patients who have a confirmed mutation of the DMD gene that is amenable to exon 53 skipping. This indication is approved under accelerated approval based on an increase in dystrophin production in skeletal muscle observed in patients treated with VILTEPSO [see Clinical Studies (14)]. Continued approval for this indication may be contingent upon verification and description of clinical benefit in a confirmatory trial.

2 DOSAGE AND ADMINISTRATION

2.1 Monitoring to Assess Safety

Serum cystatin C, urine dipstick, and urine protein-to-creatinine ratio should be measured before starting VILTEPSO. Consider measurement of glomerular filtration rate prior to initiation of VILTEPSO. Monitoring for kidney toxicity during treatment is recommended. Obtain the urine samples prior to infusion of VILTEPSO or at least 48 hours after the most recent infusion [see Warnings and Precautions (5.1)].

2.2 Dosing Information

The recommended dosage of VILTEPSO is 80 mg/kg administered once weekly as a 60-minute intravenous infusion.

If a dose of VILTEPSO is missed, it should be administered as soon as possible after the scheduled dose time.

2.3 Preparation Instructions

Parenteral drug products should be inspected visually for particulate matter and discoloration prior to administration, whenever solution and container permit. Prepare the VILTEPSO dose using aseptic technique.

1. Calculate the total dose of VILTEPSO to be administered based on the patient's weight and the recommended dosage of 80 mg/kg. Determine the volume of VILTEPSO needed and the correct number of vials to supply the full calculated dose.
2. Allow vials to warm to room temperature. Mix the contents of each vial by gently inverting 2 to 3 times. Do not shake.
3. Visually inspect each vial of VILTEPSO. VILTEPSO is a clear and colorless solution. Do not use if the solution in the vials is discolored or particulate matter is present.
4. Withdraw the calculated volume of VILTEPSO from the appropriate number of vials.
  1. If the volume of VILTEPSO required is less than 100 mL, dilution in 0.9% Sodium Chloride Injection, USP is required. Withdraw from the 100-mL infusion bag a volume of 0.9% Sodium Chloride Injection, USP, equivalent to the calculated volume of VILTEPSO and inject the VILTEPSO into the infusion bag, such that the total volume in the bag is 100 mL.
  2. If the volume of VILTEPSO required is 100 mL or more, dilution is not required, and the required amount of VILTEPSO should be placed into an empty infusion bag.
5. Visually inspect the infusion bag containing the solution for particulates. Gently invert the infusion bag to ensure equal distribution of product. Do not shake.
6. VILTEPSO contains no preservatives. Infusion should begin as soon as possible, but no more than 5 hours after preparation of VILTEPSO, and be completed within 6 hours of preparation (allowing for 1 hour of infusion time), if diluted solution is stored at 20°C to 26°C (68°F to 79°F). If immediate use is not possible, the solution may be stored for up to 24 hours at 2°C to 8°C (36°F to 46°F). Do not freeze.
7. VILTEPSO is supplied in single-dose vials. Discard unused VILTEPSO.

2.4 Administration Instructions

VILTEPSO is administered via intravenous infusion using a peripheral or central venous catheter. Flush the intravenous access line with 0.9% Sodium Chloride Injection, USP, after infusion. Filtration of VILTEPSO is not required.

Infuse VILTEPSO over 60 minutes. Do not mix other medications with VILTEPSO or infuse other medications concomitantly via the same intravenous access line. VILTEPSO should be mixed with 0.9% Sodium Chloride Injection, USP, only.

3 DOSAGE FORMS AND STRENGTHS

VILTEPSO is a clear and colorless solution available as follows:

- Injection: 250 mg/5 mL (50 mg/mL) solution in a single-dose vial

4 CONTRAINDICATIONS

None.

5 WARNINGS AND PRECAUTIONS

5.1 Kidney Toxicity

Kidney toxicity was observed in animals who received viltolarsen [see Use in Specific Populations (8.4)]. Although kidney toxicity was not observed in the clinical studies with VILTEPSO, the clinical experience with VILTEPSO is limited, and kidney toxicity, including potentially fatal glomerulonephritis, has been observed after administration of some antisense oligonucleotides. Kidney function should be monitored in patients taking VILTEPSO. Because of the effect of reduced skeletal muscle mass on creatinine measurements, serum creatinine may not be a reliable measure of kidney function in DMD patients. Serum cystatin C, urine dipstick, and urine protein-to-creatinine ratio should be measured before starting VILTEPSO. Consider also measuring glomerular filtration rate using an exogenous filtration marker before starting VILTEPSO. During treatment, monitor urine dipstick every month, and serum cystatin C and urine protein-to-creatinine ratio every three months. Only urine expected to be free of excreted VILTEPSO should be used for monitoring of urine protein. Urine obtained on the day of VILTEPSO infusion prior to the infusion, or urine obtained at least 48 hours after the most recent infusion, may be used. Alternatively, use a laboratory test that does not use the reagent pyrogallol red, as this reagent has the potential to cross react with any VILTEPSO that is excreted in the urine and thus lead to a false positive result for urine protein.

If a persistent increase in serum cystatin C or proteinuria is detected, refer to a pediatric nephrologist for further evaluation.

6 ADVERSE REACTIONS

6.1 Clinical Trials Experience

Because clinical trials are conducted under widely varying conditions, adverse reaction rates observed in the clinical trials of a drug cannot be directly compared to rates in the clinical trials of another drug and may not reflect the rates observed in practice.

In clinical trials with VILTEPSO, 32 patients have been exposed to VILTEPSO once weekly, ranging between 40 mg/kg (0.5 times the recommended dosage) and 80 mg/kg (the recommended dosage), including 16 patients treated for greater than 12 months and 8 patients treated for greater than 24 months as part of an ongoing open-label extension study. All patients were male and had genetically confirmed DMD.

Study 1 was a multicenter, 2-period, dose-finding study conducted in the United States and Canada in males 4 years to less than 10 years of age on a stable corticosteroid regimen for at least 3 months. During the initial period (first 4 weeks) of Study 1, patients were randomized (double-blind) to VILTEPSO or placebo. All patients then received 20 weeks of VILTEPSO 40 mg/kg once weekly (0.5 times the recommended dose) (N=8), or 80 mg/kg once weekly (N=8) [see Clinical Studies (14)].

Study 2 was a multicenter, parallel-group, open-label, dose-finding study conducted in Japan. Eligible patients included ambulatory and non-ambulatory males 5 years to less than 18 years of age who were assigned to receive intravenous VILTEPSO 40 mg/kg once weekly (0.5 times the recommended dose) (N=8) or 80 mg/kg once weekly (N=8) for 24 weeks.

Adverse reactions reported in ≥10% of patients treated with VILTEPSO 80 mg/kg/wk in pooled Studies 1 and 2 are displayed in Table 1. The most common adverse reactions (incidence ≥15% in patients treated with VILTEPSO) were upper respiratory tract infection, injection site reaction, cough, and pyrexia. Patients in the pooled analysis were treated with VILTEPSO for 20 to 24 weeks.

Table 1: Adverse Reactions Reported in ≥10% of DMD Patients Treated with VILTEPSO 80 mg/kg Once Weekly (Pooled Studies 1 and 2)
Adverse Reaction | VILTEPSO 80 mg/kg Once Weekly (n=16) %
Upper respiratory tract infection* | 63
Injection site reaction** | 25
Cough | 19
Pyrexia | 19
Contusion | 13
Arthralgia | 13
Diarrhea | 13
Vomiting | 13
Abdominal pain | 13
Ejection fraction decreased | 13
Urticaria | 13
* Upper respiratory tract infection includes the following terms: upper respiratory tract infection, nasopharyngitis, and rhinorrhea.
** Injection site reaction includes the following terms: injection site bruising, injection site erythema, injection site reaction, and injection site swelling.

6.2 Immunogenicity

As with all oligonucleotides, there is potential for immunogenicity. The detection of antibody formation is highly dependent on the sensitivity and specificity of the assay. Additionally, the observed incidence of antibody positivity in an assay may be influenced by several factors, including assay methodology, sample handling, timing of sample collection, concomitant medications, and underlying disease. For these reasons, comparison of the incidence of antibodies in the studies described below with the incidence of antibodies in other studies may be misleading.

For Study 1, samples collected from all 16 patients at Day 1 (pre-dose), Week 5, Week 13, and Week 24 were assessed for anti-viltolarsen antibodies. All samples were determined to be antibody negative. For the same study, serum samples collected from all 16 patients at Day 1 (pre-dose), Week 13, and Week 24 were analyzed for anti-dystrophin antibodies. Anti-dystrophin antibodies were detected in 1 out of 16 patients (6.25%) at Weeks 13 and 24; however, at Weeks 37, 49, 73, and 97, no anti-dystrophin antibodies were detected in the same patient. Further, this patient achieved a change from baseline in dystrophin levels that was comparable to the mean change in his dosage group (80 mg/kg/week) and there were no adverse events reported with this antibody production. For Study 2, all samples collected from the 16 patients were determined to be both anti-viltolarsen antibody and anti-dystrophin antibody negative. Overall, there was a lack of observed immunogenicity, which indicates that viltolarsen is not highly immunogenic.

8 USE IN SPECIFIC POPULATIONS

8.1 Pregnancy

Risk Summary

There are no human or animal data available to assess the use of VILTEPSO during pregnancy. In the U.S. general population, major birth defects occur in 2 to 4%, and miscarriage occurs in 15 to 20% of clinically recognized pregnancies.

8.2 Lactation

Risk Summary

There are no human or animal data to assess the effect of VILTEPSO on milk production, the presence of viltolarsen in milk, or the effects of VILTEPSO on the breastfed infant.

The developmental and health benefits of breastfeeding should be considered along with the mother's clinical need for VILTEPSO and any potential adverse effects on the breastfed infant from VILTEPSO or from the underlying maternal condition.

8.4 Pediatric Use

VILTEPSO is indicated for the treatment of DMD in patients who have a confirmed mutation of the DMD gene that is amenable to exon 53 skipping, including pediatric patients [see Clinical Studies (14)].

Juvenile Animal Toxicity Data

Viltolarsen (0, 15, 60, 240, or 1200 mg/kg) was administered to juvenile male mice by subcutaneous injection on postnatal day (PND) 7 and by intravenous injection weekly from PND 14 to PND 70. The highest dose resulted in deaths because of renal toxicity. In surviving animals at 240 and 1200 mg/kg, there was a dose-dependent increase in the incidence and severity of renal tubular effects (including degeneration), which were not accompanied by clinical pathology correlates. Reduced body weight gain and delayed sexual maturation were observed at the highest dose tested. At the no-effect dose for renal toxicity (60 mg/kg), plasma exposures were similar to that in humans at the recommended human dose of 80 mg/kg/week.

8.5 Geriatric Use

DMD is largely a disease of children and young adults; therefore, there is no geriatric experience with VILTEPSO.

8.6 Patients with Renal Impairment

VILTEPSO has not been studied in patients with renal impairment. Viltolarsen is mostly excreted unchanged in the urine, and renal impairment may increase its exposure. However, because of the effect of reduced skeletal muscle mass on creatinine measurements in DMD patients, no specific dosage adjustment can be recommended for DMD patients with renal impairment based on estimated glomerular filtration rate. Patients with known renal function impairment should be closely monitored during treatment with VILTEPSO.

11 DESCRIPTION

VILTEPSO (viltolarsen) injection is a sterile, preservative-free, aqueous solution for intravenous administration. VILTEPSO is a clear and colorless solution. VILTEPSO is supplied in single-dose vials containing 250 mg/5 mL viltolarsen (50 mg/mL) in 0.9% sodium chloride. Each milliliter of VILTEPSO contains 50 mg viltolarsen and 9 mg sodium chloride in water for injection. The final product is adjusted to a pH ranging between 7.0 and 7.5 using hydrochloric acid and/or sodium hydroxide.

Viltolarsen is an antisense oligonucleotide of the phosphorodiamidate morpholino oligomer (PMO) subclass. PMOs are synthetic molecules in which the five-membered ribofuranosyl rings found in natural DNA and RNA are replaced by a six-membered morpholino ring. Each morpholino ring is linked through an uncharged phosphorodiamidate moiety rather than the negatively charged phosphate linkage that is present in natural DNA and RNA. Each phosphorodiamidate morpholino subunit contains one of the heterocyclic bases found in DNA (adenine, cytosine, guanine, or thymine). Viltolarsen contains 21 linked subunits. The molecular formula of viltolarsen is C244H381N113O88P20 and the molecular weight is 6924.82 daltons. The structure and base sequence of viltolarsen are shown in Figure 1.

Figure 1: Structural Formula of Viltolarsen

12 CLINICAL PHARMACOLOGY

12.1 Mechanism of Action

VILTEPSO is designed to bind to exon 53 of dystrophin pre-mRNA resulting in exclusion of this exon during mRNA processing in patients with genetic mutations that are amenable to exon 53 skipping. Exon 53 skipping is intended to allow for production of an internally truncated dystrophin protein in patients with genetic mutations that are amenable to exon 53 skipping.

12.2 Pharmacodynamics

After treatment with VILTEPSO 80 mg/kg once weekly, all patients evaluated (N=8) were found to produce mRNA for a truncated dystrophin protein, as measured by reverse transcription polymerase chain reaction (RT-PCR), and demonstrated exon 53 skipping, as measured by DNA sequence analysis.

In Study 1, all patients who received VILTEPSO 80 mg/kg once weekly for 20 to 24 weeks showed an increase from baseline in dystrophin protein expression, as quantified by a validated Western blot method (mean 5.3%; median 3.8%; range 0.7% to 13.9% of normal levels when normalized to myosin heavy chain; p-value 0.01). Mass spectrometry, immunofluorescence staining, and RT-PCR results were supportive of the Western blot data [see Clinical Studies (14)]. Expected localization of truncated dystrophin to the sarcolemma in muscle fibers of patients treated with viltolarsen was confirmed by immunofluorescence staining.

12.3 Pharmacokinetics

The pharmacokinetics of viltolarsen was evaluated in DMD patients following administration of intravenous (IV) doses ranging from 1.25 mg/kg/week (0.016 times the recommended dosage) to 80 mg/kg/week (the recommended dosage). Viltolarsen exposure increased proportionally with dose, with minimal accumulation with once-weekly dosing. Inter-subject variability (as %CV) for Cmax and AUC ranged from 16% to 27% respectively.

VILTEPSO is administered as an IV infusion over 60 minutes. Bioavailability is assumed to be 100%, and median Tmax was around 1 hour (end of infusion).

Distribution

The mean viltolarsen steady-state volume of distribution was 300 mL/kg (%CV=14 at a dose of 80 mg/kg. Viltolarsen plasma protein binding ranged from 39% to 40% and is not concentration dependent.

Elimination

Metabolism

Data from in vitro metabolism indicate that viltolarsen is metabolically stable. No metabolites were detected in plasma or urine.

Excretion

VILTEPSO is excreted mainly as an unchanged drug in the urine. Viltolarsen elimination half-life was 2.5 (%CV=8) hours, and plasma clearance was 217 mL/hr/kg (%CV=22).

Specific Populations

Age, Sex & Race

The pharmacokinetics of viltolarsen have been evaluated only in male pediatric DMD patients.There is no experience with VILTEPSO in patients 65 years of age or older. No marked differences in any PK parameters were observed between White and Asian patients.

Patients with Renal or Hepatic Impairment

VILTEPSO has not been studied in patients with renal or hepatic impairment. Viltolarsen was found to be metabolically stable, and hepatic metabolism does not contribute to the elimination of viltolarsen. In addition, viltolarsen was mainly excreted unchanged in the urine. Viltolarsen is eliminated renally, and renal impairment is expected to result in increasing exposure of viltolarsen. However, because of the effect of reduced skeletal muscle mass on creatinine measurements in DMD patients, no specific dosage adjustment can be recommended for DMD patients with renal impairment based on glomerular filtration rate estimated by serum creatinine [see Use in Specific Populations (8.6)].

In Vitro Drug Interaction Studies

Viltolarsen did not inhibit CYP3A4/5, CYP1A2, CYP2A6, CYP2B6, CYP2C8, CYP2C9, CYP2C19, CYP2D6, CYP2E1, UGT1A1, or UGT2B7. Viltolarsen did not induce CYP1A2, CYP2B6, or CYP3A4.

Viltolarsen is not metabolized by CYP enzymes and is not a substrate of transporters BCRP, BSEP, MDR1, OAT1, OAT3, OCT1, OCT2, MATE1, or MATE2-K. Viltolarsen did not inhibit the transporters tested (OATP1B1, OATP1B3, OAT3, BCRP, MDR1, BSEP, OAT1, OCT1, OCT2, MATE1, and MATE2-K).

Based on in vitro data, viltolarsen has a low potential for drug-drug interactions with major CYP enzymes and drug transporters in humans.

13 NONCLINICAL TOXICOLOGY

13.1 Carcinogenesis, Mutagenesis, Impairment of Fertility

Carcinogenesis

Carcinogenicity studies of viltolarsen have not been conducted.

Mutagenesis

Viltolarsen was negative for genotoxicity in in vitro (bacterial reverse mutation, chromosomal aberration in Chinese hamster lung cells) and in vivo (mouse bone marrow micronucleus) assays.

Impairment of Fertility

Intravenous administration of viltolarsen (0, 60, 240, or 1000 mg/kg) to male mice weekly prior to and during mating to untreated females did not have adverse effects on fertility. Plasma exposure (AUC) at the highest dose was approximately 18 times that in humans at the recommended human dose of 80 mg/kg/week.

14 CLINICAL STUDIES

The effect of VILTEPSO on dystrophin production was evaluated in one study in DMD patients with a confirmed mutation of the DMD gene that is amenable to exon 53 skipping (Study 1; NCT02740972).

Study 1 was a multicenter, 2-period, dose-finding study conducted in the United States and Canada.

During the initial period (first 4 weeks) of Study 1, patients were randomized (double blind) to VILTEPSO or placebo. All patients then received 20 weeks of open-label VILTEPSO 40 mg/kg once weekly (0.5 times the recommended dosage) (N=8) or 80 mg/kg once weekly (N=8). Study 1 enrolled ambulatory male patients 4 years to less than 10 years of age (median age 7 years) on a stable corticosteroid regimen for at least 3 months.

Efficacy was assessed based on change from baseline in dystrophin protein level (measured as % of the dystrophin level in healthy subjects, i.e., % of normal) at Week 25. Muscle biopsies (left or right biceps brachii) were collected from patients at baseline and following 24 weeks of VILTEPSO treatment, and analyzed for dystrophin protein level by Western blot normalized to myosin heavy chain (primary endpoint) and mass spectrometry (secondary endpoint).

In patients who received VILTEPSO 80 mg/kg once weekly, mean dystrophin levels increased from 0.6% (SD 0.8) of normal at baseline to 5.9% (SD 4.5) of normal by Week 25, with a mean change in dystrophin of 5.3% (SD 4.5) of normal levels (p=0.01) as assessed by validated Western blot (normalized to myosin heavy chain); the median change from baseline was 3.8%. All patients demonstrated an increase in dystrophin levels over their baseline values. As assessed by mass spectrometry (normalized to filamin C), mean dystrophin levels increased from 0.6% (SD 0.2) of normal at baseline to 4.2% (SD 3.7) of normal by Week 25, with a mean change in dystrophin of 3.7% (SD 3.8) of normal levels (nominal p=0.03, not adjusted for multiple comparisons); the median change from baseline was 1.9%.

Individual patient dystrophin levels in patients evaluated in Study 1 are shown in Figure 2 and Table 2.

Figure 2: Dystrophin Expression in Individual Patients (Study 1)

Patients Treated With VILTEPSO 80 mg/kg/week (n=8)

Note: Solid lines represent individual patient data. Dystrophin was measured using Western blot and normalized to myosin heavy chain.

Table 2: Dystrophin Expression in Individual Patients (Study 1)
Patient Number | Western Blot % Normal Dystrophina
Patient Number | Baseline | Week 25 | Change from Baseline
1 | 0.46 | 1.14 | 0.69
2 | 0.40 | 3.97 | 3.57
3 | 0.46 | 2.97 | 2.51
4 | 0.09 | 10.40 | 10.31
5 | 0.51 | 14.42 | 13.91
6 | 2.61 | 7.40 | 4.79
7 | 0.43 | 3.06 | 2.63
8 | 0.09 | 4.07 | 3.98
a Data were normalized by myosin heavy chain

16 HOW SUPPLIED/STORAGE AND HANDLING

16.1 How Supplied

VILTEPSO injection is supplied in single-dose vials. The solution is clear and colorless.

- Single-dose vials containing 250 mg/5 mL (50 mg/mL) viltolarsen NDC 73292-011-01

16.2 Storage and Handling

Store VILTEPSO at 2°C to 8°C (36°F to 46°F). Do not freeze.

17 Patient Counseling Information

Kidney Toxicity

Inform patients nephrotoxicity has occurred with drugs similar to VILTEPSO. Advise patients of the importance of monitoring for kidney toxicity by their healthcare providers during treatment with VILTEPSO [see Warnings and Precautions (5.1)].

Manufactured for:
NS Pharma, Inc.
Paramus, NJ 07652

Principal Display Panel – Carton Label

NDC 73292-011-01

Rx only

Viltepso

(viltolarsen) injection

250 mg/5 mL (50 mg/mL)

For intravenous infusion

Must be refrigerated,
store at 2°C to 8°C

(36°F to 46°F)

Do not freeze

Single dose

1 vial

Principal Display Panel – Vial Label

NDC 73292-011-01

Viltepso

(viltolarsen) injection

250 mg/5 mL (50 mg/mL)

For intravenous infusion

Refrigerate at 2°C to 8°C (36°F to 46°F)

Mfg for: NS Pharma, Inc.

Rx only